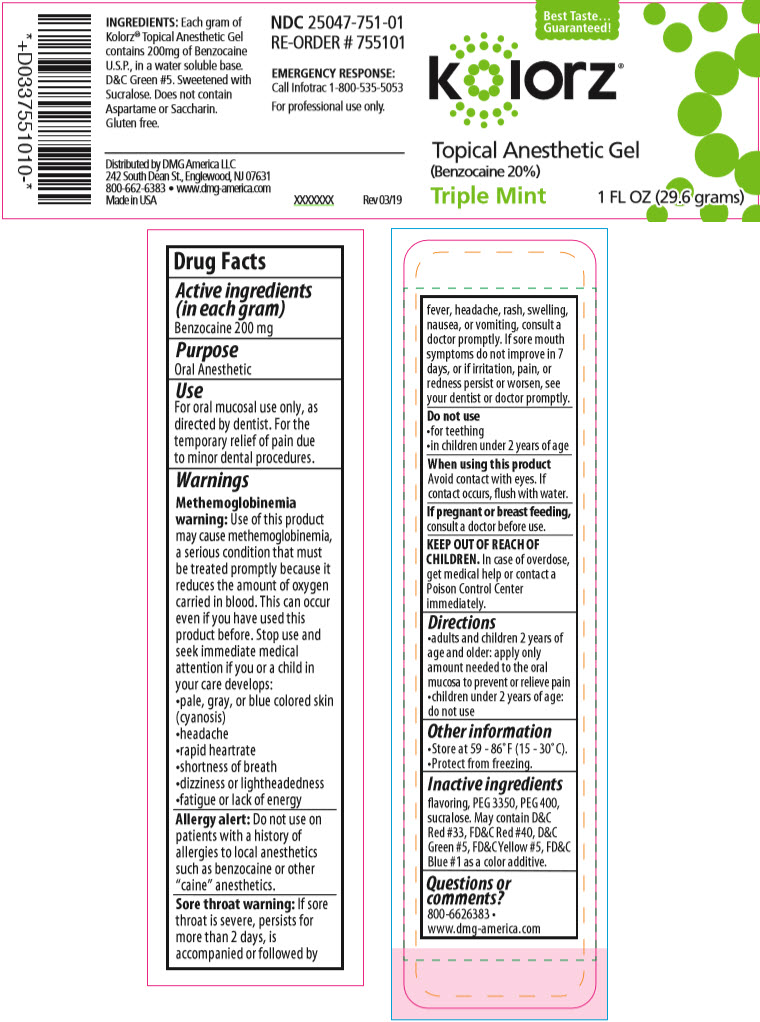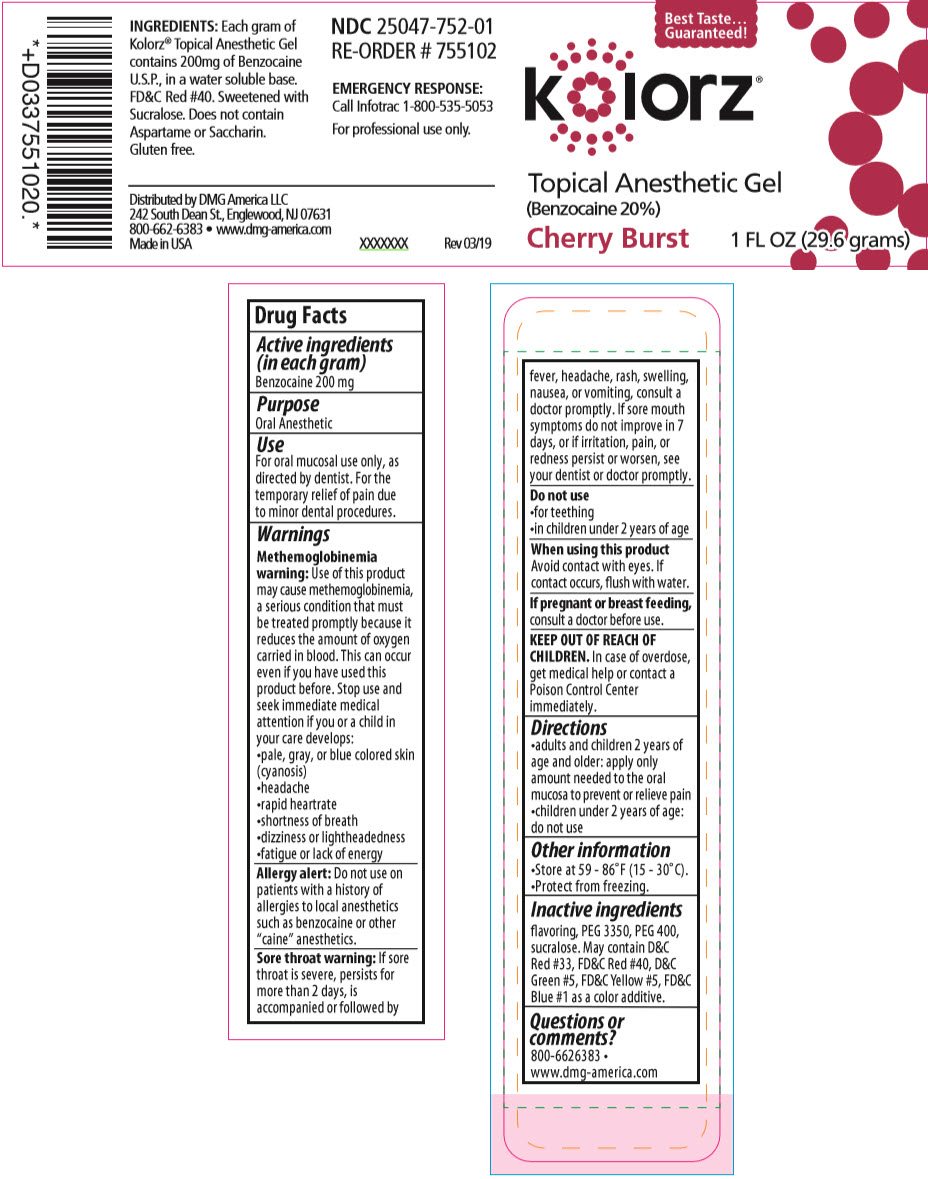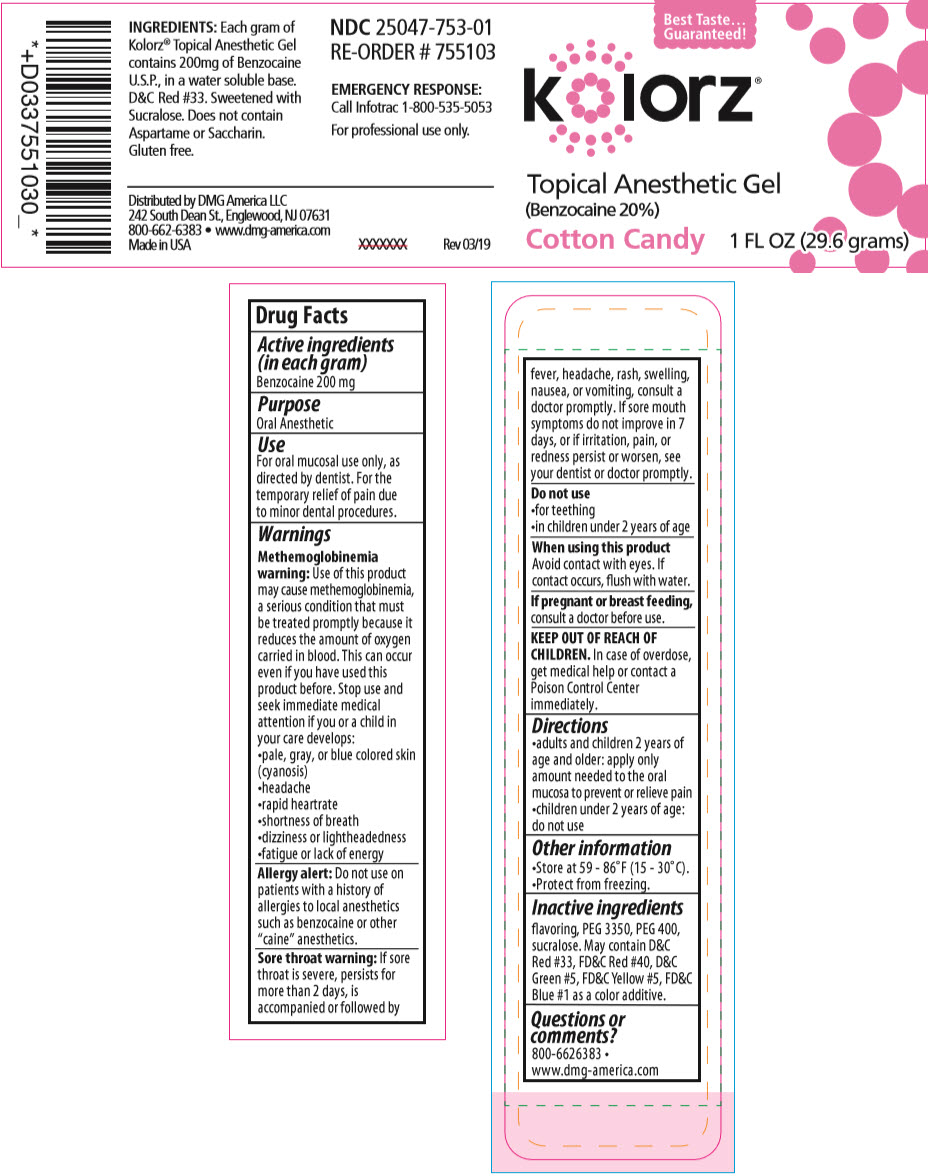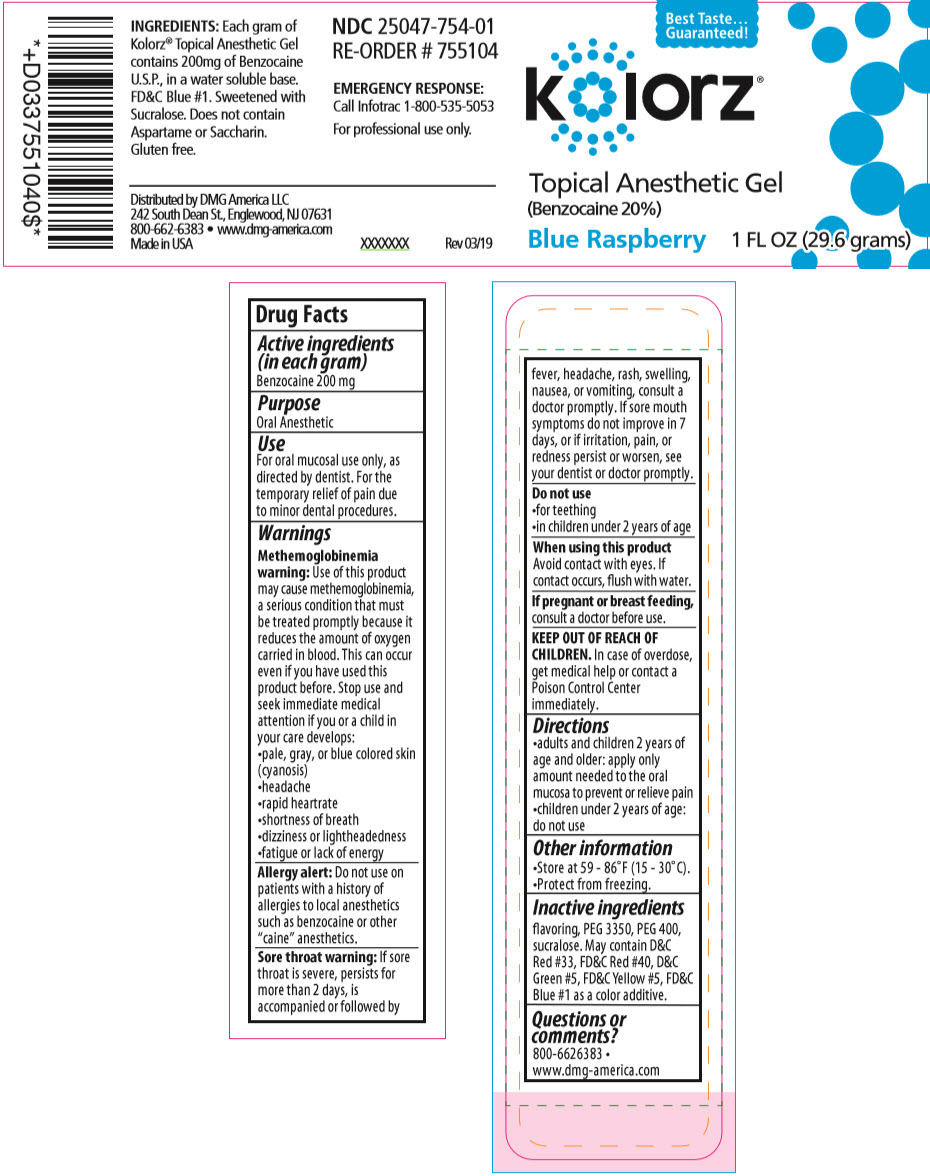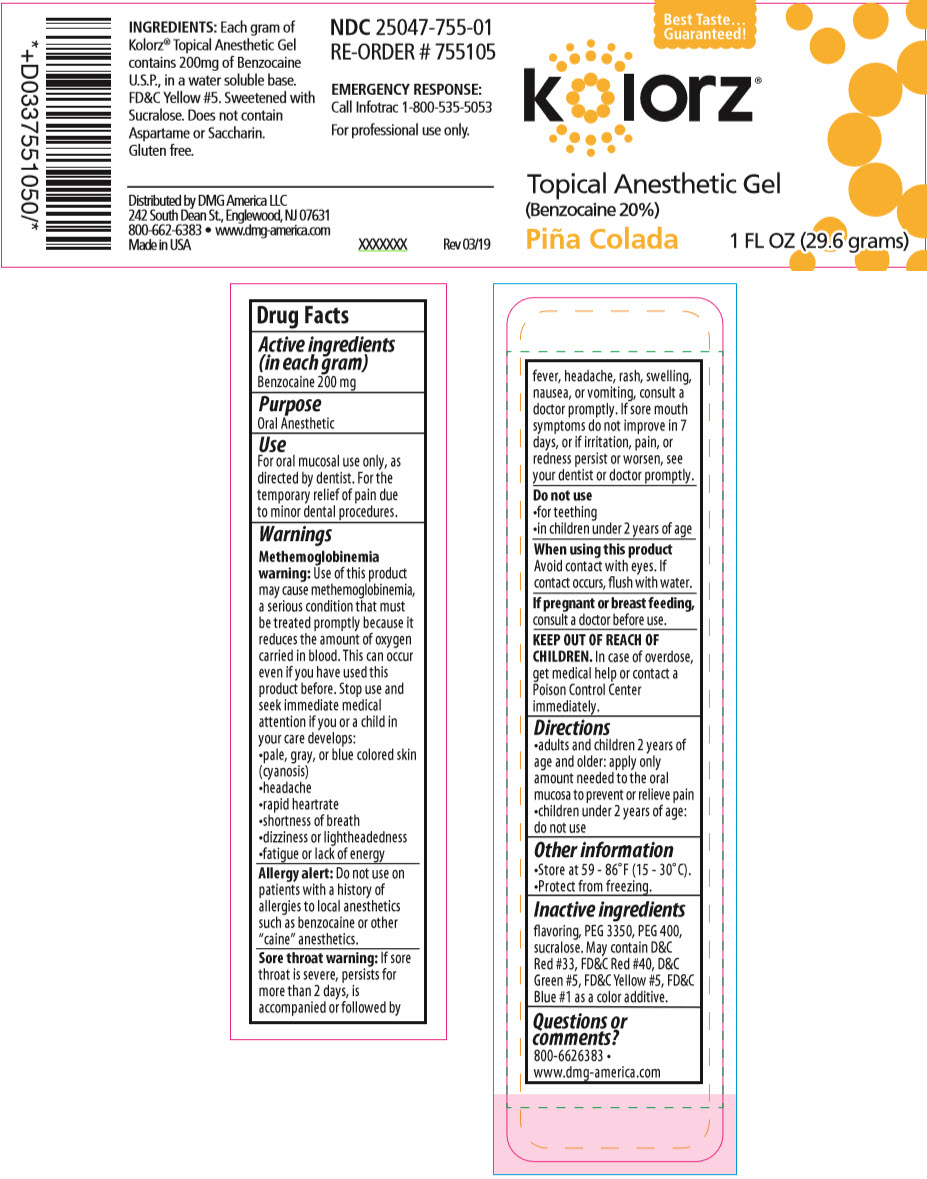 DRUG LABEL: KOLORZ TOPICAL ANESTHETIC
NDC: 25047-751 | Form: GEL
Manufacturer: DMG AMERICA, LLC
Category: otc | Type: HUMAN OTC DRUG LABEL
Date: 20211001

ACTIVE INGREDIENTS: BENZOCAINE 200 mg/1 g
INACTIVE INGREDIENTS: POLYETHYLENE GLYCOL 3350; POLYETHYLENE GLYCOL 400; SUCRALOSE; D&C RED NO. 33; FD&C RED NO. 40; D&C GREEN NO. 5; FD&C YELLOW NO. 5; FD&C BLUE NO. 1

KOLORZ® TOPICAL ANESTHETIC

Drug Facts

Active ingredients (in each gram)

Benzocaine 200 mg

Purpose

Oral Anesthetic

Use

For oral mucosal use only, as directed by dentist. For the temporary relief of pain due to minor dental procedures.

Warnings

Methemoglobinemia warning

Use of this product may cause methemoglobinemia, a serious condition that must be treated promptly because it reduces the amount of oxygen carried in blood. This can occur even if you have used this product before. Stop use and seek immediate medical attention if you or a child in your care develops:

- pale, gray, or blue colored skin (cyanosis)
- headache
- rapid heartrate
- shortness of breath
- dizziness or lightheadedness
- fatigue or lack of energy

Allergy alert

Do not use on patients with a history of allergies to local anesthetics such as benzocaine or other "caine" anesthetics.

Sore throat warning

If sore throat is severe, persists for more than 2 days, is accompanied or followed by fever, headache, rash, swelling, nausea, or vomiting, consult a doctor promptly. If sore mouth symptoms do not improve in 7 days, or if irritation, pain, or redness persist or worsen, see your dentist or doctor promptly.

Do not use

- for teething
- in children under 2 years of age

When using this product

Avoid contact with eyes. If contact occurs, flush with water.

PREGNANCY OR BREAST FEEDING

If pregnant or breast feeding, consult a doctor before use.

KEEP OUT OF REACH OF CHILDREN. In case of overdose, get medical help or contact a Poison Control Center immediately.

Directions

- adults and children 2 years of age and older: apply only amount needed to the oral mucosa to prevent or relieve pain
- children under 2 years of age: do not use

Other information

- Store at 59 - 86°F (15 - 30°C).
- Protect from freezing.

Inactive ingredients

flavoring, PEG 3350, PEG 400, sucralose. May contain D&C Red #33, FD&C Red #40, D&C Green #5, FD&C Yellow #5, FD&C Blue #1 as a color additive.

Questions or comments?

800-6626383 • www.dmg-america.com

Distributed by DMG America LLC
242 South Dean St., Englewood, NJ 07631

PRINCIPAL DISPLAY PANEL - 29.6 grams Bottle Label - Triple Mint

Best Taste...
Guaranteed!

kolorz®

Topical Anesthetic Gel
(Benzocaine 20%)
Triple Mint

1 FL OZ (29.6 grams)

PRINCIPAL DISPLAY PANEL - 29.6 grams Bottle Label - Cherry Burst

Best Taste...
Guaranteed!

kolorz®

Topical Anesthetic Gel
(Benzocaine 20%)
Cherry Burst

1 FL OZ (29.6 grams)

PRINCIPAL DISPLAY PANEL - 29.6 grams Bottle Label - Cotton Candy

Best Taste...
Guaranteed!

kolorz®

Topical Anesthetic Gel
(Benzocaine 20%)
Cotton Candy

1 FL OZ (29.6 grams)

PRINCIPAL DISPLAY PANEL - 29.6 grams Bottle Label - Blue Raspberry

Best Taste...
Guaranteed!

kolorz®

Topical Anesthetic Gel
(Benzocaine 20%)
Blue Raspberry

1 FL OZ (29.6 grams)

PRINCIPAL DISPLAY PANEL - 29.6 grams Bottle Label - Piña Colada

Best Taste...
Guaranteed!

kolorz®

Topical Anesthetic Gel
(Benzocaine 20%)
Piña Colada

1 FL OZ (29.6 grams)